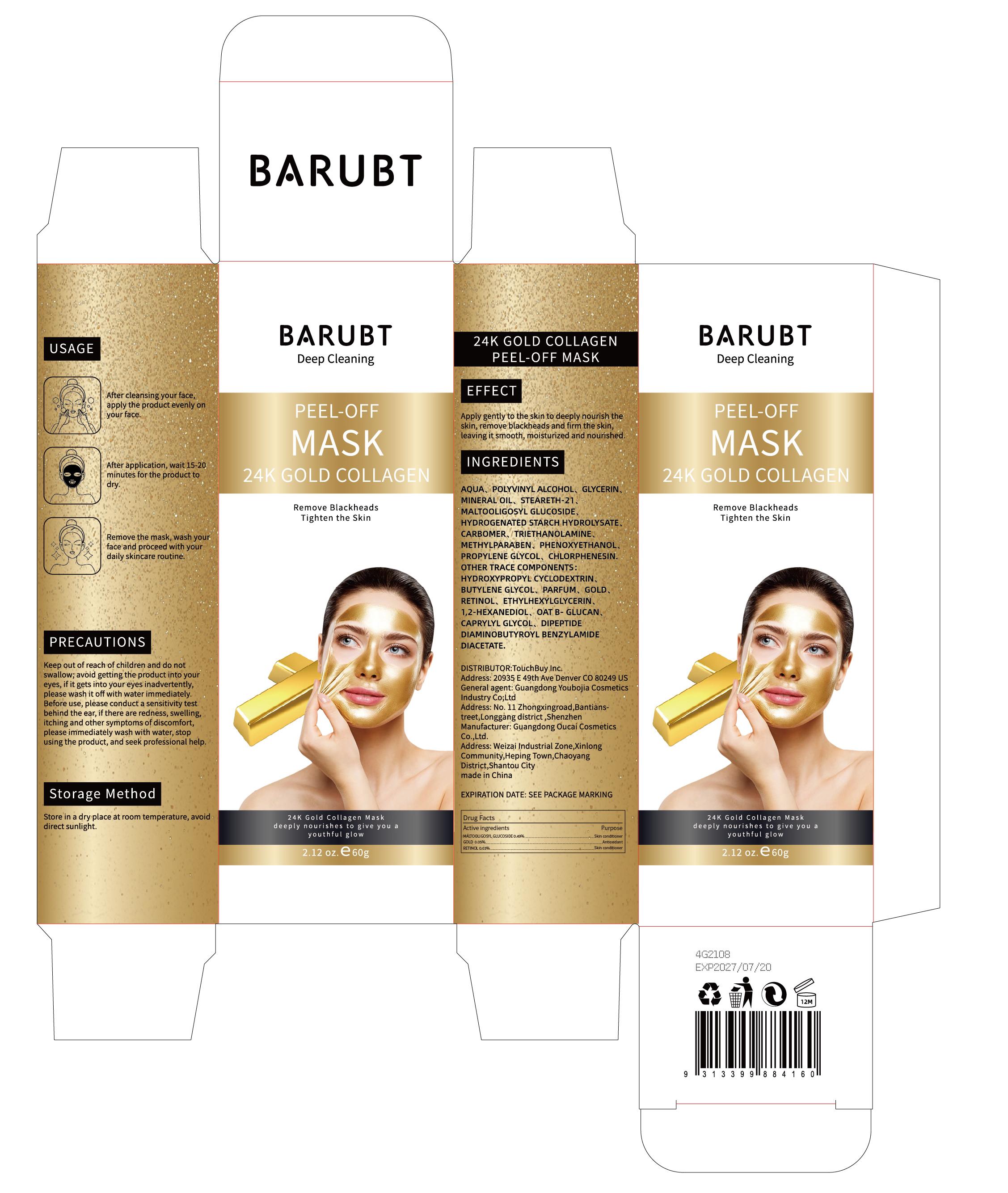 DRUG LABEL: BARUBT 24K GOLD COLLAGEN  PEEL-OFF MASK
NDC: 84712-015 | Form: PASTE
Manufacturer: Guangdong Youbaijia Cosmetic Industry Co., Ltd
Category: otc | Type: HUMAN OTC DRUG LABEL
Date: 20240917

ACTIVE INGREDIENTS: RETINOL 0.018 g/60 g; GOLD 0.03 g/60 g; MALTOOLIGOSYL GLUCOSIDE 0.294 g/60 g
INACTIVE INGREDIENTS: MINERAL OIL 1.8 g/60 g; GLYCERIN 3 g/60 g

ACTIVE INGREDIENT

MALTOOLIGOSYL GLUCOSIDE 0.49%
GOLD 0.05%
RETINOL 0.03%

INACTIVE INGREDIENT

AQUA
POLYVINYL ALCOHOL
GLYCERIN
MINERAL OIL
STEARETH-21
HYDROGENATED STARCH HYDROLYSATE
CARBOMER
TRIETHANOLAMINE
METHYLPARABEN
PHENOXYETHANOL
PROPYLENE GLYCOL
CHLORPHENESIN
HYDROXYPROPYL CYCLODEXTRIN
BUTYLENE GLYCOL
PARFUM
ETHYLHEXYLGLYCERIN
1,2-HEXANEDIOL
OAT B-GLUCAN
CAPRYLYL GLYCOL
DIPEPTIDE DIAMINOBUTYROYL BENZYLAMIDE DIACETATE

Do not use on damaged skin.

Keep out of reach of children and do not swallow

PURPOSE

Remove Blackheads,Tighten the Skin

QUESTIONS

Contact name: Jessie Peng
Company phone number: +1 818 579 7288
Company e-mail: jessie@registeragentllc.com

WHEN USING

keep out of eyes. Rinse with water to remove.

STOP USE

if there are redness, swelling itching and other symptoms of discomfort,please.immediately wash with water, stop using the product, and seek professional help

DOSAGE AND ADMINISTRATION

- After cleansing your face,apply the product evenly on your face.
- After application, wait 15-20 minutes for the product to dry
- Remove the mask, wash your face and proceed with your daily skincare routine.

STORAGE AND HANDLING

Store in a dry place at room temperature, avoid direct sunlight.

INDICATIONS AND USAGE

Apply gently to the skin to deeply nourish the skin, remove blackheads and firm the skin,leavingit smooth, moisturized and nourished

WARNINGS

For external use only.